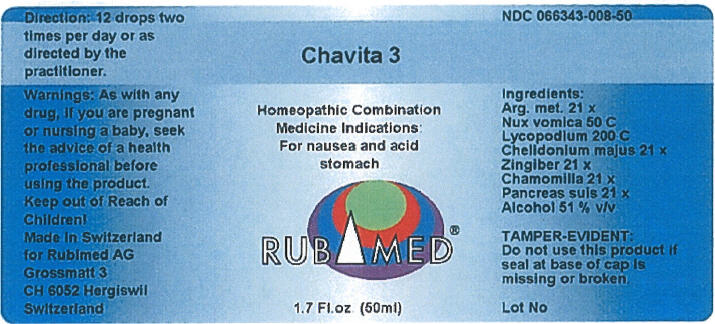 DRUG LABEL: Chavita 3
NDC: 66343-008 | Form: LIQUID
Manufacturer: RUBIMED AG
Category: otc | Type: HUMAN OTC DRUG LABEL
Date: 20150706

ACTIVE INGREDIENTS: Silver Cyanide 21 [hp_X]/1 mL; Strychnos Nux-Vomica Seed 50 [hp_C]/1 mL; Lycopodium Clavatum Spore 200 [hp_C]/1 mL; Chelidonium majus 21 [hp_X]/1 mL; Ginger 21 [hp_X]/1 mL; Matricaria Recutita 21 [hp_X]/1 mL; Sus Scrofa Pancreas 21 [hp_X]/1 mL
INACTIVE INGREDIENTS: Alcohol 0.51 mL/1 mL

Chavita 3

INDICATIONS AND USAGE

PURPOSE

Homeopathic Combination Medicine Indications: For nausea and acid stomach

Ingredients

INACTIVE INGREDIENT

Arg. met. 21 x
Nux vomica 50 C
Lycopodium 200 C
Chelidonian majus 21 x
Zingiber 21 x
Chamomilla 21 x
Pancreas suis 21 x
Alcohol 51 % v/v

TAMPER-EVIDENT

Do not use this product if seal at base of cap is missing or broken.

Direction

12 drops two times per day or as directed by the practitioner.

Warnings

PREGNANCY OR BREAST FEEDING

As with any drug, if you are pregnant or nursing a baby, seek the advice of a health professional before using the product.

Keep out of Reach of Children!

PRINCIPAL DISPLAY PANEL - 50 ml Bottle Label

Chavita 3

Homeopathic Combination
Medicine Indications:
For nausea and acid
stomach

RUBIMED®

1.7 Fl.oz. (50 ml)